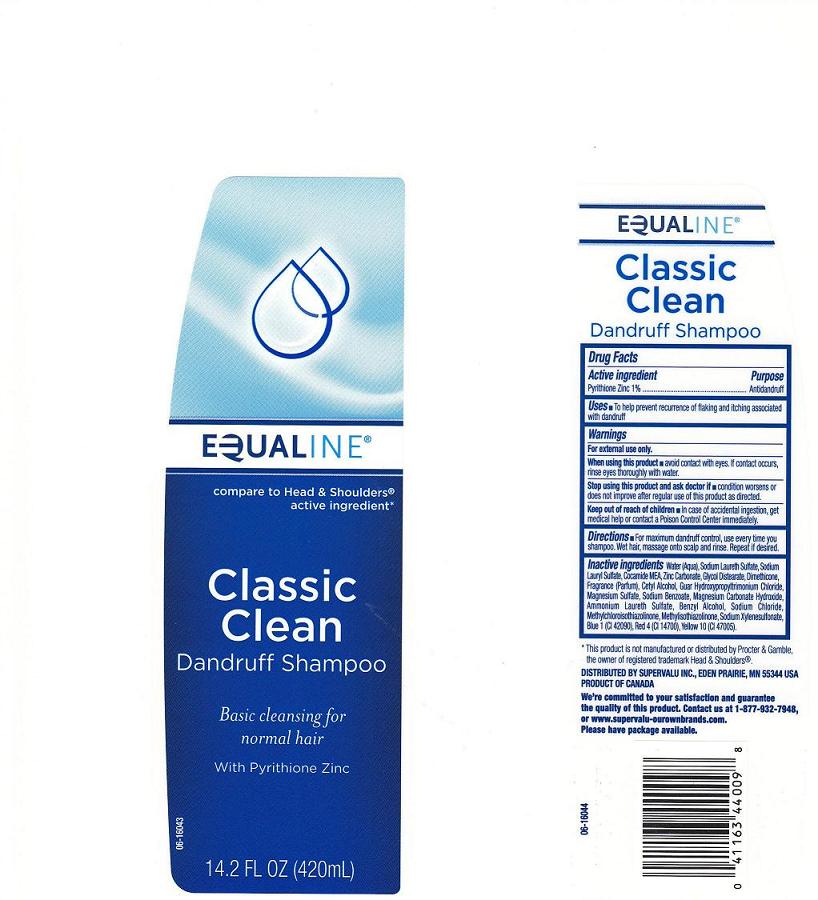 DRUG LABEL: Equaline Dandruff
NDC: 41163-413 | Form: SHAMPOO
Manufacturer: Supervalu Inc
Category: otc | Type: HUMAN OTC DRUG LABEL
Date: 20100916

ACTIVE INGREDIENTS: PYRITHIONE ZINC 1 mL/100 mL

Drug Facts Box - Back Label

ACTIVE INGREDIENT

PYRITHIONE ZINC 1%

PURPOSE

ANTI-DANDRUFF

WARNINGS

FOR EXTERNAL USE ONLY

WHEN USING THIS PRODUCT

AVOID CONTACT WITH EYES. IF CONTACT OCCURS, RINSE EYES THROUGHLY WITH WATER.

STOP USE AND ASK A DOCTOR IF

CONDITION WORSENS OR DOES NOT IMPROVE AFTER REGULAR USE OF THIS PRODUCT AS DIRECTED

KEEP OUT OF REACH OF CHILDREN

IN CASE OF ACCIDENTAL INGESTION, GET MEDICAL HELP OR CONTACT POISON CONTROL CENTER IMMEDIATELY.

Uses

HELPS PREVENT RECURRENCE OF FLAKING AND ITCHING ASSOCIATED WITH DANDRUFF

Directions

FOR MAXIMUM DANDRUFF CONTROL, USE EVERY TIME YOU SHAMPOO. WET HAIR, MASSAGE ONTO SCALP AND RINSE. REPEAT IF DESIRE.

Inactive Ingredients

Water (Aqua), Sodium Laureth Sulfate, Sodium Lauryl Sulfate, Cocamide MEA, Zinc Carbonate, Glycol Distearate, Dimethicone, Fragrance (Parfum), Cetyl Alcohol, Guar Hydroxypropyltrimonium Chloride, Magnesium Sulfate, Sodium Benzoate, Magnesium Carbonate Hydroxide, Ammonium Laureth Sulfate, Benzyl Alcohol, Sodium Chloride, Methylchloroisothiazolinone, Methylisothiazolinone, Sodium Xylene Sulfonate, Blue 1 (CI 42090), Red 4 (CI 14700), Yellow 10 (CI 47005).

Package Front and Back Labels

eql14.jpg